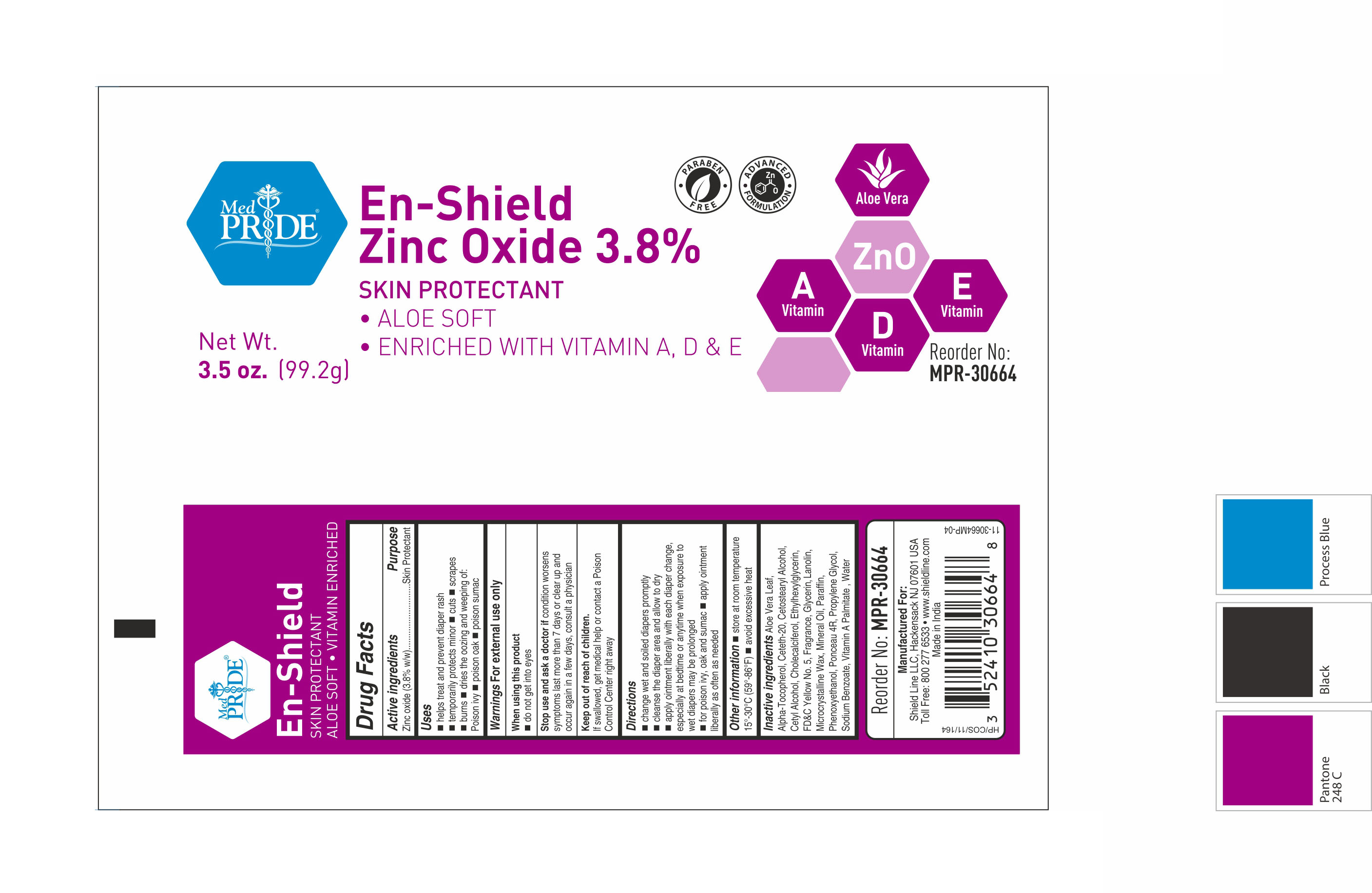 DRUG LABEL: MedPride
NDC: 52410-3066 | Form: CREAM
Manufacturer: Shield Line LLC
Category: otc | Type: HUMAN OTC DRUG LABEL
Date: 20250815

ACTIVE INGREDIENTS: ZINC OXIDE 3.8 g/100 g
INACTIVE INGREDIENTS: ALPHA-TOCOPHEROL; CETOSTEARYL ALCOHOL; CETYL ALCOHOL; CHOLECALCIFEROL; GLYCERIN; WATER; SODIUM BENZOATE; CETETH-20; ALOE VERA LEAF; LANOLIN; MINERAL OIL; PARAFFIN; MICROCRYSTALLINE WAX; PHENOXYETHANOL; PROPYLENE GLYCOL; FD&C YELLOW NO. 5; PONCEAU 4R; VITAMIN A PALMITATE; ETHYLHEXYLGLYCERIN

MedPride Enshield

Active Ingredient

Zinc Oxide (3.8%w/w)

Purpose

Skin Protectant

Uses

■ helps treat and prevent diaper rash ■ temporarily protects minor ■ cuts ■ scrapes ■ burns dries the oozing and weeping of: ■ Poison ivy ■ poison oak ■ poison sumac

Warnings

For external use only

When using this product

■ do not get into eyes

Stop Use and ask a doctor if

conditions worsen symptoms last more than 7 days or clear up and occur again in a few days, consult a physician

Keep out of reach of children

If swallowed, get medical help or contact a Poison Control Center right away.

Directions

■ change wet and soiled diapers promptly ■ cleanse the diaper area and allow to dry ■ apply ointment liberally with each diaper change, especially at bedtime or anytime when exposure to wet diapers may be prolonged ■ for poison ivy, oak and sumac ■ apply ointment liberally as needed

Other Information

■ store at room temperature 15-30C (59-86F) ■ avoid excessive heat

Inactive ingredients

Aloe Vera Leaf, Alpha-Tocopherol, Ceteth-20, Cetostearyl Alcohol, Cetyl Alcohol, Cholecalciferol, Ethylhexylglycerin,FD&C Yellow No. 5, Fragrance, Glycerin, Lanolin, Microcrystalline Wax, Mineral Oil, Paraffin, Phenoxyethanol, Ponceau 4R, Propylene Glycol, Sodium Benzoate, Vitamin A Palmitate, Water